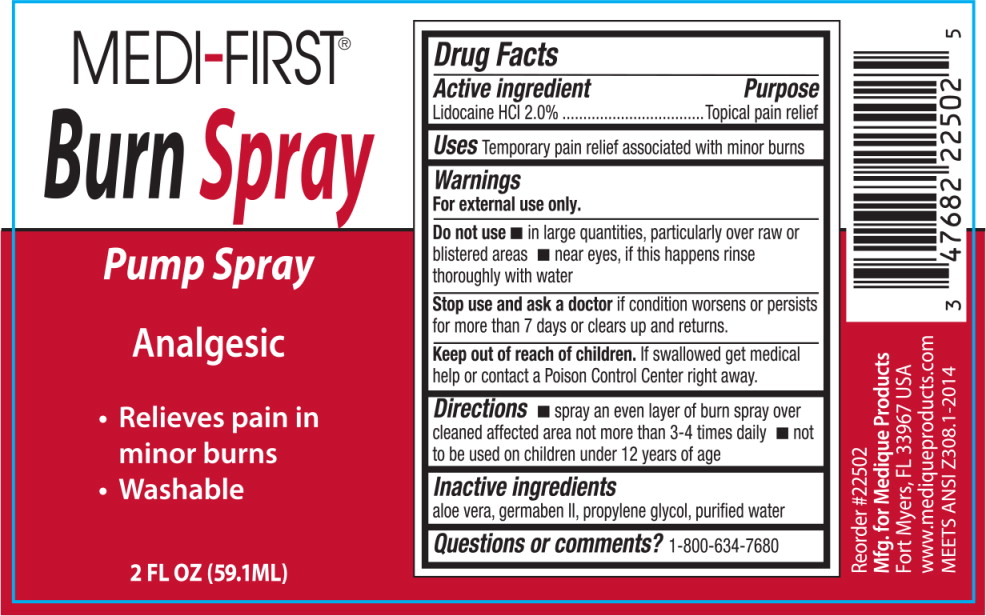 DRUG LABEL: MediFirst Burn
NDC: 47682-225 | Form: SPRAY
Manufacturer: Unifirst First Aid Corporation
Category: otc | Type: HUMAN OTC DRUG LABEL
Date: 20250908

ACTIVE INGREDIENTS: LIDOCAINE HYDROCHLORIDE 20 g/1 L
INACTIVE INGREDIENTS: ALOE VERA LEAF; PROPYLENE GLYCOL; DIAZOLIDINYL UREA; WATER; PROPYLPARABEN; METHYLPARABEN

Medi-First Burn Spray

Active ingredient

Lidocaine HCl 2.0%

Purpose

Topical pain relief

Uses

Temporary pain relief associated with minor burns

Warnings

For external use only.

Do not use

- In large quantities, particularly over raw or blistered areas
- near eyes, if this happens rinse thoroughly with water

Stop use and ask doctor if

condition worsens or persists for more than 7 days or clears up and returns.

Keep out of reach of children. If swallowed get medical help or contact a Poison Control Center right away.

Directions

- spray an even layer of burn spray over cleaned affected area not more than 3-4 times daily
- not to be used on children under 12 years of age

Inactive ingredients

aloe vera, germaben II, propylene glycol, purified water

Questions or Comments?

1-800-634-7680

Medi-First Burn Spray Label

MEDI-FIRST®

Burn Spray

Pump Spray

Analgesic

- Relieves pain in minor burns
- Washable

2 FL OZ (59.1ML)